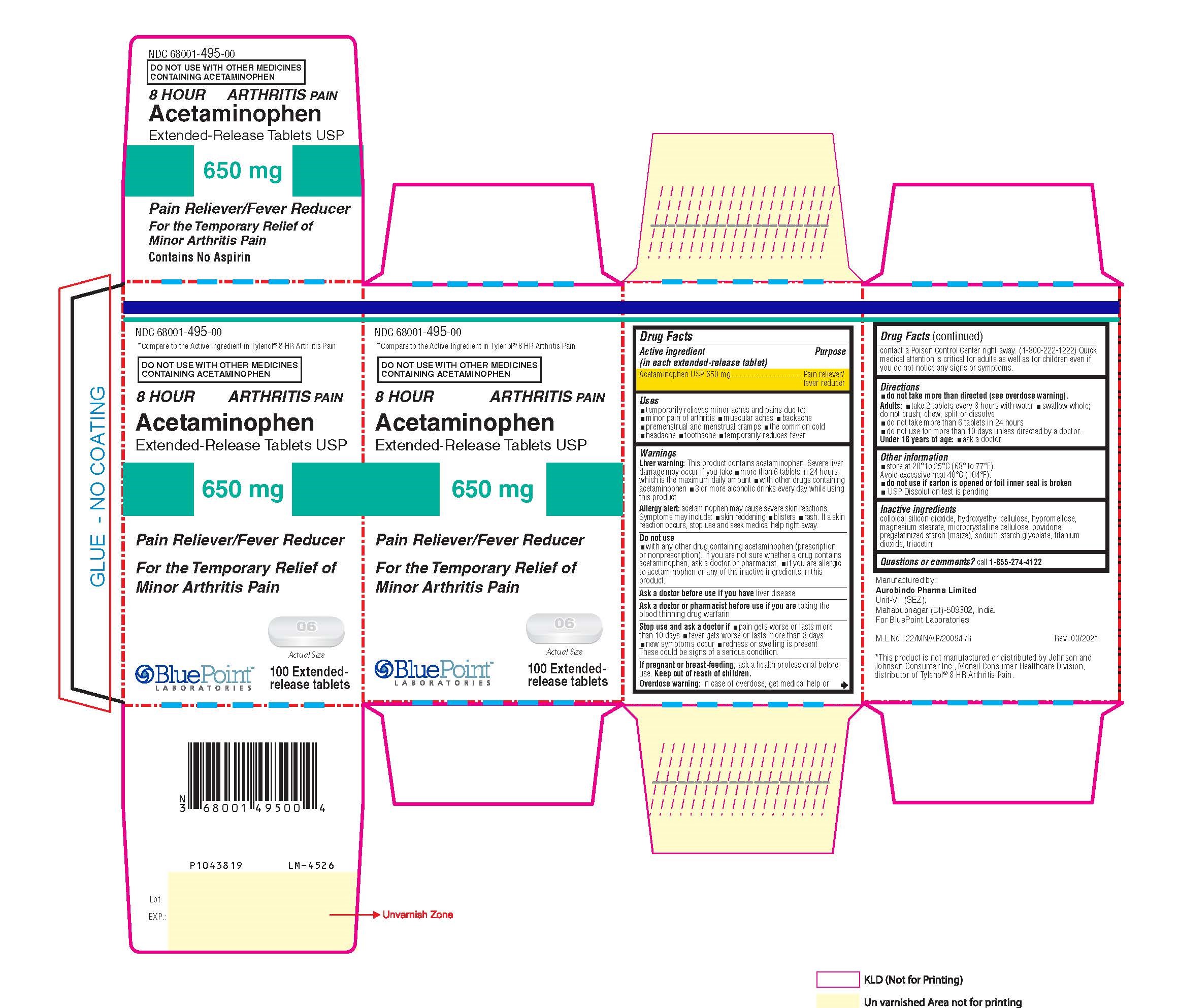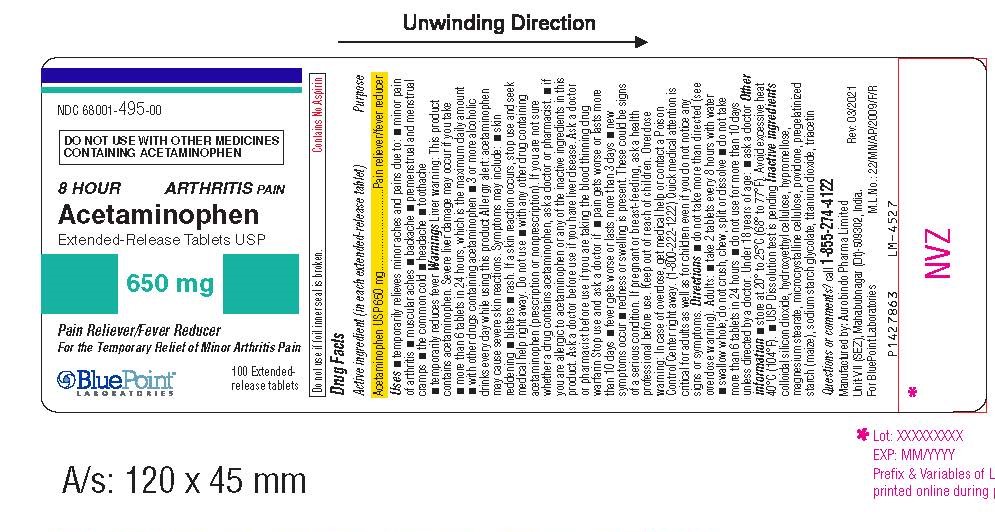 DRUG LABEL: Acetaminophen
NDC: 68001-495 | Form: TABLET
Manufacturer: BluePoint Laboratories
Category: otc | Type: HUMAN OTC DRUG LABEL
Date: 20240605

ACTIVE INGREDIENTS: ACETAMINOPHEN 650 mg/1 1
INACTIVE INGREDIENTS: STARCH, CORN; TITANIUM DIOXIDE; TRIACETIN; SILICON DIOXIDE; POVIDONE, UNSPECIFIED; HYDROXYETHYL CELLULOSE (140 MPA.S AT 5%); MICROCRYSTALLINE CELLULOSE; SODIUM STARCH GLYCOLATE TYPE B POTATO; HYPROMELLOSE, UNSPECIFIED; MAGNESIUM STEARATE

Acetaminophen Extended-Release Tablets, USP 650mg

Drug Facts

Active Ingredient (in each extended release tablet)

Acetaminophen USP 650 mg

Purpose

Pain reliever/fever reducer

Uses

- temporarily relieves minor aches and pains due to:
- minor pain of arthritis
- muscular aches
- backache
- premenstrual and menstrual cramps
- the common cold
- headache
- toothache
- temporarily reduces fever

Warnings

Liver warning: This product contains acetaminophen. Severe liver damage may occur if you take

- more than 6 tablets in 24 hours, which is the maximum daily amount
- with other drugs containing acetaminophen
- 3 or more alcoholic drinks every day while using this product

Allergy alert: acetaminophen may cause severe skin reactions. Symptoms may include:

- skin reddening
- blisters
- rash

If a skin reaction occurs, stop use and seek medical help right away.

Do not use

- with any other drug containing acetaminophen (prescription or nonprescription). If you are not sure

whether a drug contains acetaminophen, ask a doctor or pharmacist.

- if you are allergic to acetaminophen or any of the inactive ingredients in this product.

Ask a doctor before ue if you have liver disease.

Ask a doctor or pharmacist before use if you are taking the blood thinning drug warfarin

Stop use and ask a doctor if

- pain gets worse or lasts more than 10 days
- fever gets worse or lasts more than 3 days
- new symptoms occur
- redness or swelling is present

These could be signs of a serious condition.

If pregnant or breast-feeding, ask a health professional before use.

Keep out of reach of children.

Overdose warning: In case of overdose, get medical help or contact a Poison Control Center right

away. (1-800-222-1222) Quick medical attention is critical for adults as well as for children even if you

do not notice any signs or symptoms.

Directions

do not take more than directed (see overdose warning).

Adults:

- take 2 tablets every 8 hours with water
- swallow whole; do not crush, chew, split or dissolve
- do not take more than 6 tablets in 24 hours
- do not use for more than 10 days unless directed by a doctor.

Under 18 years of age:

- ask a doctor

Other information

- store at 20º to 25ºC (68º to 77ºF). Avoid excessive heat 40ºC (104ºF)
- do not use if carton is opened or foil inner seal is broken
- USP Dissolution test is pending

Inactive ingredients

colloidal silicon dioxide, hydroxyethyl cellulose, hypromellose, magnesium stearate, microcrystalline

cellulose, povidone, pregelatinized starch (maize), sodium starch glycolate, titanium dioxide, triacetin

Questions or comments?

call 1-855-274-4122

Manufactured by:
Aurobindo Pharma Limited
Unit-VII (SEZ), Mahabubnagar (Dt)-509302, India.

For BluePoint Laboratories

Rev: 03/2021

M.L. No.: 22/MN/AP/2009/F/R

Package Label - Principal Display Panel

Acetaminophen Extended-Release tablets USP 650mg (100 tablets Carton) NDC: 68001-495-00

Acetaminophen Extended-Release tablets USP 650mg (100 tablets Container Label) NDC: 68001-495-00